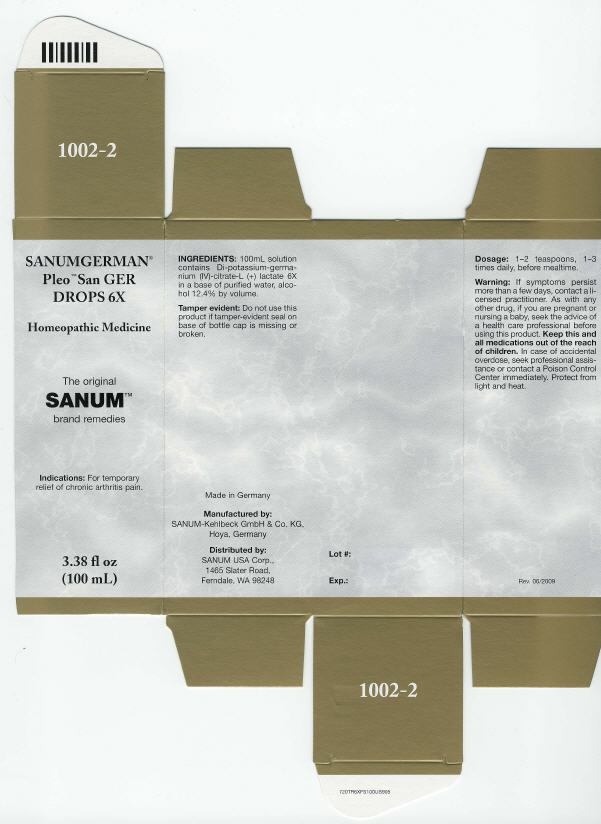 DRUG LABEL: Pleo San Ger
NDC: 60681-1002 | Form: SOLUTION/ DROPS
Manufacturer: Sanum Kehlbeck GmbH & Co. KG
Category: homeopathic | Type: HUMAN OTC DRUG LABEL
Date: 20100803

ACTIVE INGREDIENTS: Germanium Citrate Lactate 6 [hp_X]/100 mL
INACTIVE INGREDIENTS: water; alcohol

SANUMGERMAN®
Pleo™ San GER
DROPS 6X

Homeopathic Medicine

3.38 fl oz
(100 mL)

Indications

For temporary relief of chronic arthritis pain.

INGREDIENTS

100mL solution contains Di-potassium-germanium (IV)-citrate-L (+) lactate 6X in a base of purified water, alcohol 12.4% by volume.

Tamper evident

Do not use this product if tamper-evident seal on base of bottle cap is missing or broken.

Dosage

1–2 teaspoons, 1–3 times daily, before mealtime.

Warning

If symptoms persist more than a few days, contact a licensed practitioner. As with any other drug, if you are pregnant or nursing a baby, seek the advice of a health care professional before using this product.

KEEP OUT OF REACH OF CHILDREN

Keep this and all medications out of the reach of children. In case of accidental overdose, seek professional assistance or contact a Poison Control Center immediately.

STORAGE AND HANDLING

Protect from light and heat.

Made in Germany

Manufactured by:
SANUM-Kehlbeck GmbH & Co. KG,
Hoya, Germany

Distributed by:
SANUM USA Corp.,
1465 Slater Road,
Ferndale, WA 98248

Rev. 06/2009

PRINCIPAL DISPLAY PANEL - 100 mL Bottle Carton

SANUMGERMAN®
Pleo™ San GER
DROPS 6X

Homeopathic Medicine

The original
SANUM™
brand remedies

Indications: For temporary
relief of chronic arthritis pain.

3.38 fl oz
(100 mL)